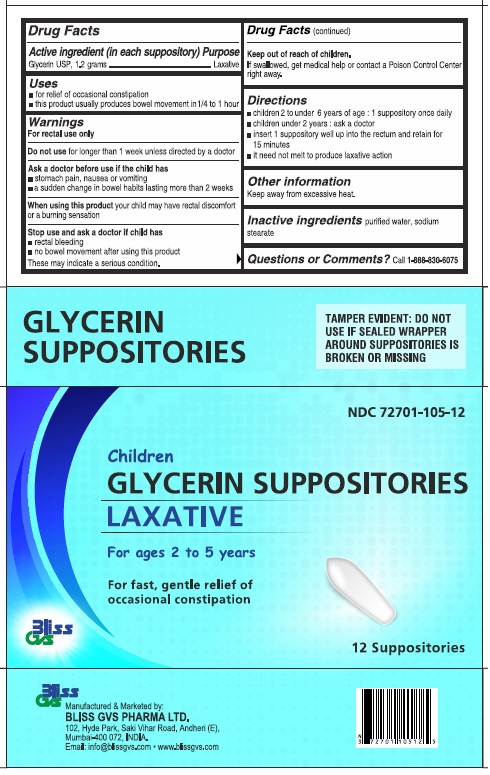 DRUG LABEL: Bliss GVS


NDC: 72701-105 | Form: SUPPOSITORY
Manufacturer: Bliss GVS Pharma Limited
Category: otc | Type: HUMAN OTC DRUG LABEL
Date: 20241017

ACTIVE INGREDIENTS: GLYCERIN 1.2 g/1 1
INACTIVE INGREDIENTS: WATER; SODIUM STEARATE

Bliss Glycerin Suppositories, Children

Drug Facts

Active ingredient (in each suppository)

Glycerin USP, 1.2 grams

Purpose

Laxative

Uses

- for relief of occasional constipation
- this product usually produces bowel movement in 1/4 to 1 hour

Warnings

For rectal use only

DO NOT USE

Do not usefor longer than one week unless directed by a doctor

Ask a doctor before use if the child has

- abdominal pain, nausea or vomiting
- a sudden change in bowel habits lasting more than 2 weeks

WHEN USING

When using this productyour child may have rectal discomfort or a burning sensation

Stop use and ask a doctor if the child has

- rectal bleeding
- no bowel movement after using this product

These may indicate a serious condition.

Keep out of reach of children.If swallowed, get medical help or contact a Poison Control Center right away.

Directions

- children 2 to under 6 years of age: 1 suppository once daily
- children under 2 years: ask a doctor
- insert suppository well up into rectum and retain for 15 minutes
- it need not melt to produce laxative action

Other information

keep away from excessive heat.

Inactive ingredientspurified water, sodium stearate

Questions or Comments?Call 1-888-830-6075

TAMPER EVIDENT: DO NOT USE IF SEALED WRAPPER AROUND SUPPOSITORIES IS BROKEN OR MISSING

Manufactured and Marketed by:

BLISS GVS PHARMA LTD.

102, Hyde Park, Saki Vihar Road, Andheri (E)

Mumbai-400 072, INDIA

Email: info@blissgvs.com • www.blissgvs.com

PACKAGE LABEL

NDC 72701-105-12

Children GLYCERIN SUPPOSITORIES

LAXATIVE

For ages 2 to 5 years

For fast, gentle relief of occasional constipation

12 Suppositories